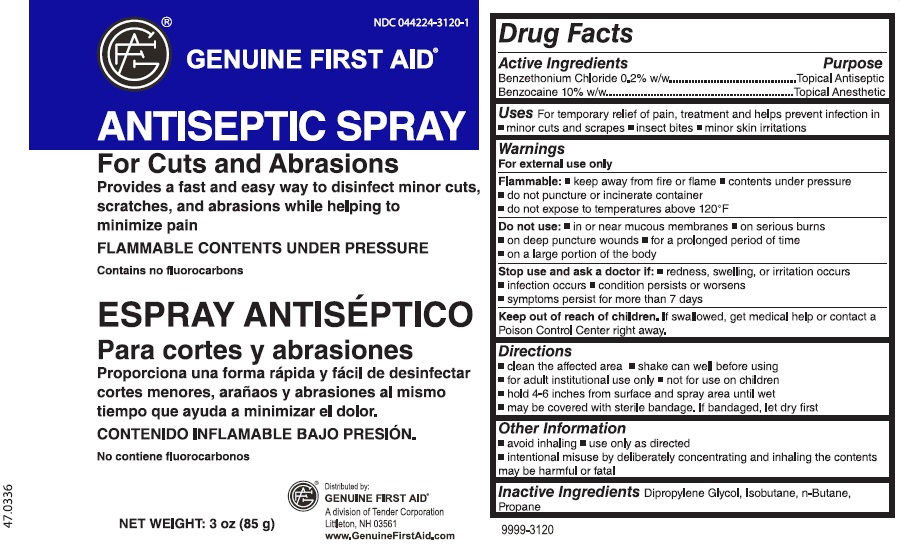 DRUG LABEL: Benzocaine and Benzethonium
NDC: 44224-3120 | Form: AEROSOL, SPRAY
Manufacturer: Tender Corporation
Category: otc | Type: HUMAN OTC DRUG LABEL
Date: 20160621

ACTIVE INGREDIENTS: BENZETHONIUM CHLORIDE 170 mg/85 g; BENZOCAINE 8500 mg/85 g
INACTIVE INGREDIENTS: PROPANE; DIPROPYLENE GLYCOL; ISOBUTANE; BUTANE

Genuine First Aid Antiseptic Spray

Active Ingredients

Benzethonium Chloride 0.2% w/w

Benzocaine 10% w/w

Purpose

Topical Antiseptic

Topical Anesthetic

Uses

For temporary relief of pain, treatment and helps prevent infection in

- minor cuts and scrapes
- insect bites
- minor skin irritations

Warnings

For external use only

Flammable:

- keep away from fire or flame
- contents under pressure
- do not puncture or incinerate container
- do not expose to temperatures above 120°F

Do not use:

- in or near mucous membranes
- on serious burns
- on deep puncture wounds
- for a prolonged period of time
- on a large portion of the body

Stop use and ask a doctor if:

- redness, swelling, or irritation occurs
- infection occurs
- condition persists or worsens
- symptoms persists for more than 7 days

Keep out of reach of children.

If swallowed, get medical help or contact a Poison Control Center right away.

Directions

- clean the affected area
- shake can well before using
- for adult institutional use only
- not for use on children
- hold 4-6 inches from surface and spray area until wet
- may be covered with sterile bandage. If bandaged, let dry first

Other Information

- avoid inhaling
- use only as directed
- intentional misuse by deliberately concentrating and inhaling the contents may be harmful or fatal

Inactive Ingredients

Dipropylene Glycol, Isobutane, n-Butane, Propane